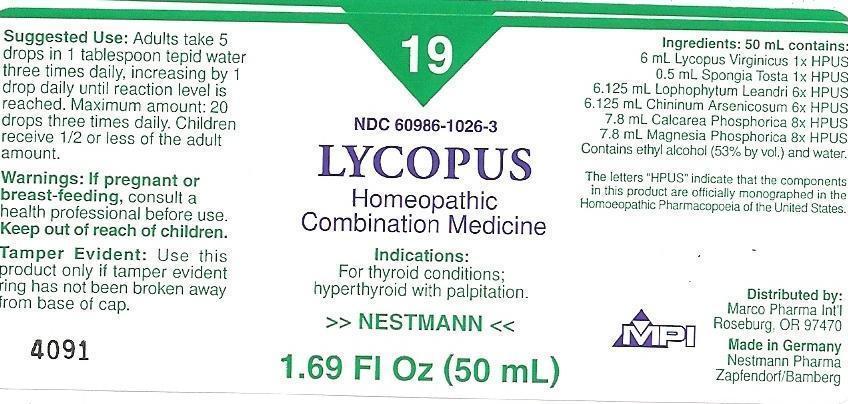 DRUG LABEL: LYCOPUS
NDC: 60986-1026 | Form: LIQUID
Manufacturer: Marco Pharma International LLC.
Category: homeopathic | Type: HUMAN OTC DRUG LABEL
Date: 20150707

ACTIVE INGREDIENTS: LYCOPUS VIRGINICUS 1 [hp_X]/100 mL; SPONGIA OFFICINALIS SKELETON, ROASTED 1 [hp_X]/100 mL; LOPHOPHYTUM LEANDRII 6 [hp_X]/100 mL; QUININE ARSENITE 6 [hp_X]/100 mL; TRIBASIC CALCIUM PHOSPHATE 8 [hp_X]/100 mL; MAGNESIUM PHOSPHATE, DIBASIC TRIHYDRATE 8 [hp_X]/100 mL
INACTIVE INGREDIENTS: ALCOHOL; WATER

Drug Facts

Active Ingredients

LYCOPUS VIRGINICUS 1XHPUS

SPONGIA TOSTA 1XHPUS

LOPHOPHYTUM LEANDRII 6XHPUS

CHININUM ARSENICOSUM 6XHPUS

CALCAREA PHOSPHORICA 8XHPUS

MAGNESIA PHOSPHORICA 8XHPUS

The letters HPUS indicates that the components in this product are officially monographed in the Homeopathic Pharmacopoeia of United Sates.

Purpose

FOR THYROID CONDITIONS; HYPERTHYROID WITH PALPITATION.

Keep out of reach of children.

Suggested use

ADULTS TAKE 5 DROPS IN 1 TABLESPOON TEPID WATER THREE TIME DAILY, INCREASING BY 1 DROP DAILY UNTIL REACTION LEVEL IS REACHED. MAXIMUM AMOUNT: 20 DROPS THREE TIMES DAILY. CHILDREN RECEIVE 1/2 OR LESS OF THE ADULT AMOUNT.

Warnings

If pregnant or breast-feeding, consult a health professional before use.

DOSAGE AND ADMINISTRATION

(Read Suggested Use Section)

Inactive Ingredients

CONTAINS ETHYL ALCOHOL (53% BY VOL.) AND WATER